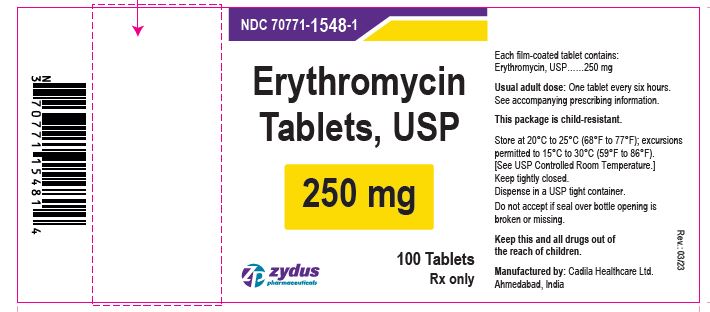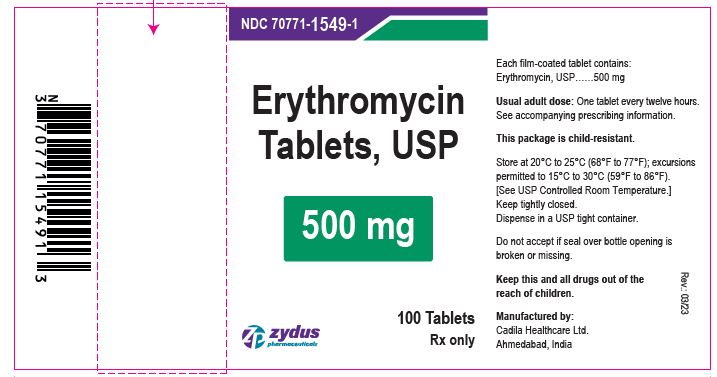 DRUG LABEL: Erythromycin
NDC: 70771-1548 | Form: TABLET, FILM COATED
Manufacturer: Zydus Lifesciences Limited
Category: prescription | Type: HUMAN PRESCRIPTION DRUG LABEL
Date: 20230621

ACTIVE INGREDIENTS: ERYTHROMYCIN 250 mg/1 1
INACTIVE INGREDIENTS: ALUMINUM OXIDE; CELLULOSE, MICROCRYSTALLINE; CROSCARMELLOSE SODIUM; CROSPOVIDONE; D&C RED NO. 30; FERRIC OXIDE RED; FERRIC OXIDE YELLOW; HYDROXYPROPYL CELLULOSE (90000 WAMW); HYPROMELLOSE 2910 (6 MPA.S); HYPROMELLOSE PHTHALATE (31% PHTHALATE, 40 CST); MAGNESIUM STEARATE; POLYETHYLENE GLYCOL 6000; POVIDONE K30; POVIDONE K90; PROPYLENE GLYCOL; SILICON DIOXIDE; SODIUM HYDROXIDE; SORBIC ACID; SORBITAN MONOOLEATE; TALC; TITANIUM DIOXIDE; TRISODIUM CITRATE DIHYDRATE

Erytrhomycin Tablets, USP

PACKAGE LABEL.PRINCIPAL DISPLAY PANEL

NDC 70771-1548-1 in bottle of 100 tablets

Erythromycin Tablets USP, 250 mg

Rx only

100 tablets

NDC 70771-1549-1 in bottle of 100 tablets

Erythromycin Tablets USP, 500 mg

Rx only

100 tablets